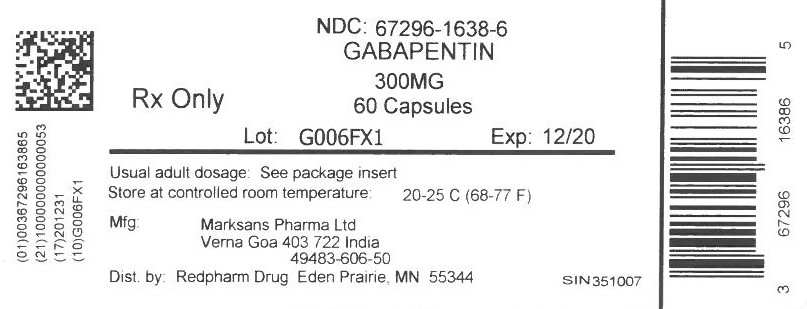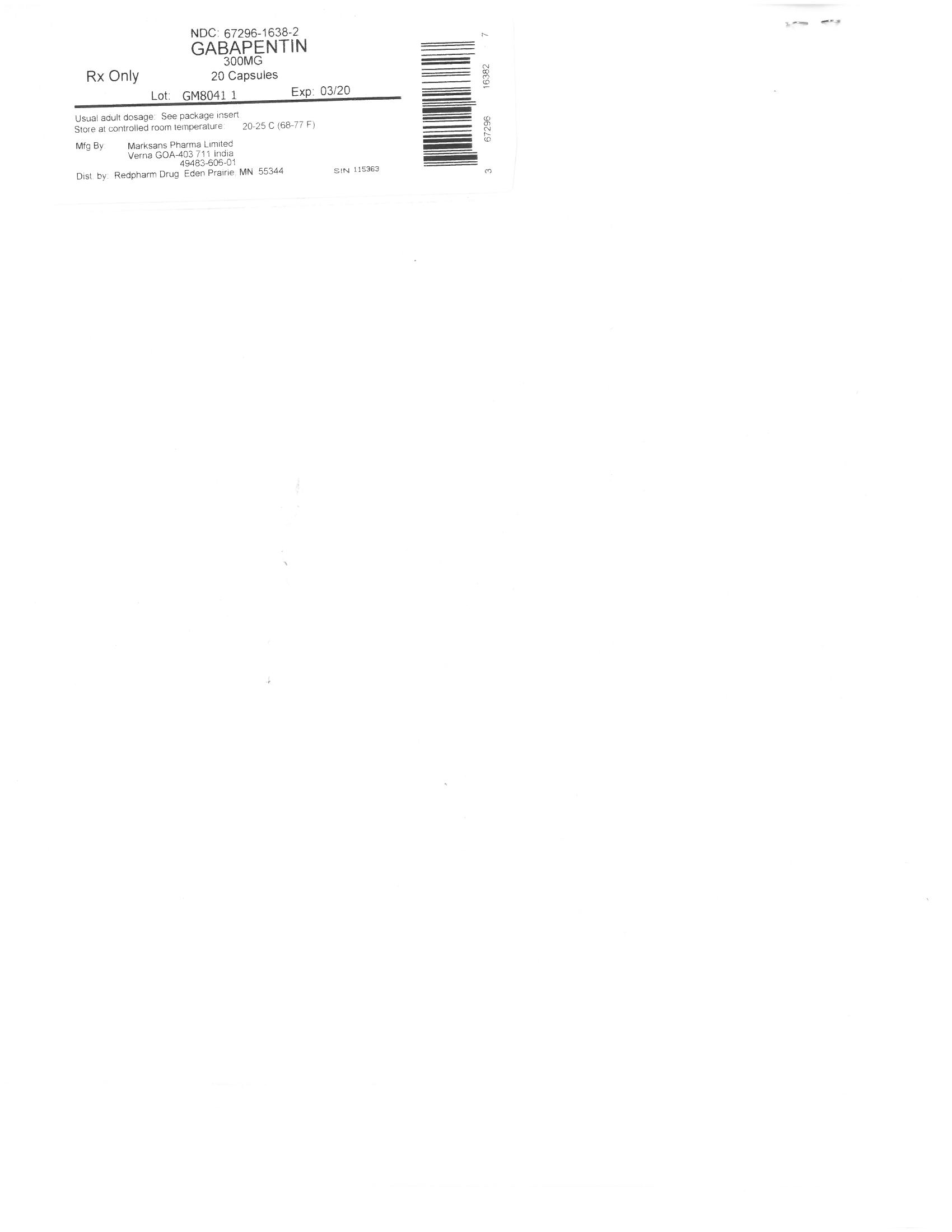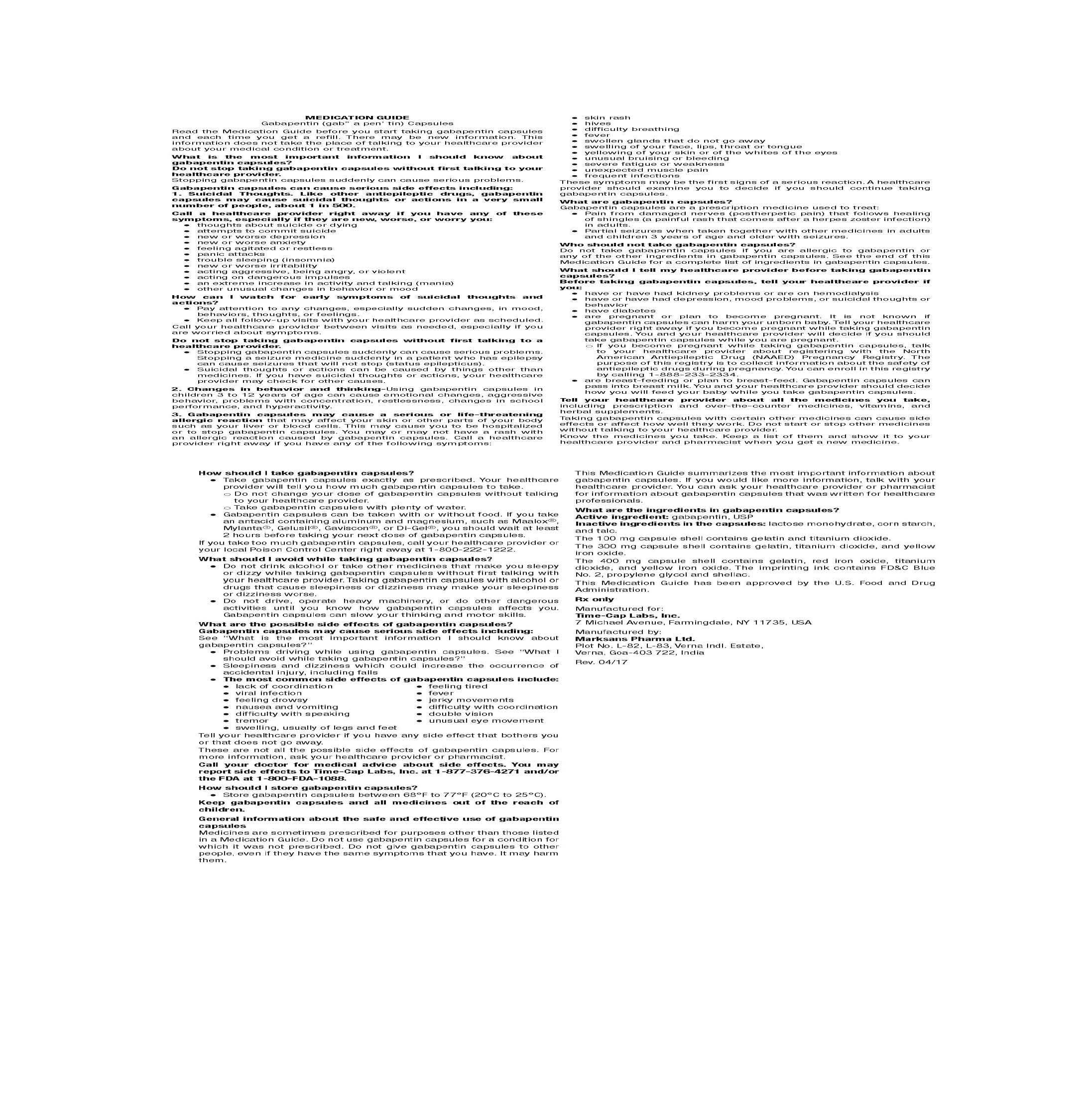 DRUG LABEL: GABAPENTIN
NDC: 67296-1638 | Form: CAPSULE
Manufacturer: RedPharm Drug, Inc.
Category: prescription | Type: HUMAN PRESCRIPTION DRUG LABEL
Date: 20210113

ACTIVE INGREDIENTS: GABAPENTIN 300 mg/1 1
INACTIVE INGREDIENTS: STARCH, CORN; TALC; LACTOSE MONOHYDRATE; GELATIN; TITANIUM DIOXIDE; FERRIC OXIDE YELLOW; PROPYLENE GLYCOL; SHELLAC

GABAPENTIN 300MG

HOW SUPPLIED

100 mg Capsules (White/White colored, size '3' hard gelatin capsules with "103" printed on body of capsules containing white to off white granular powder) Bottles of 100 & 500

HOW SUPPLIED

300 mg Capsules (Yellow/Yellow colored, size '1' hard gelatin capsules with "104" printed on body of capsules containing white to off white granular powder) Bottles of 100 & 500

HOW SUPPLIED

400 mg Capsules (Orange/Orange colored, size '0' hard gelatin capsules with "105" printed on body of capsules containing white to off white granular powder) Bottles of 100 & 500